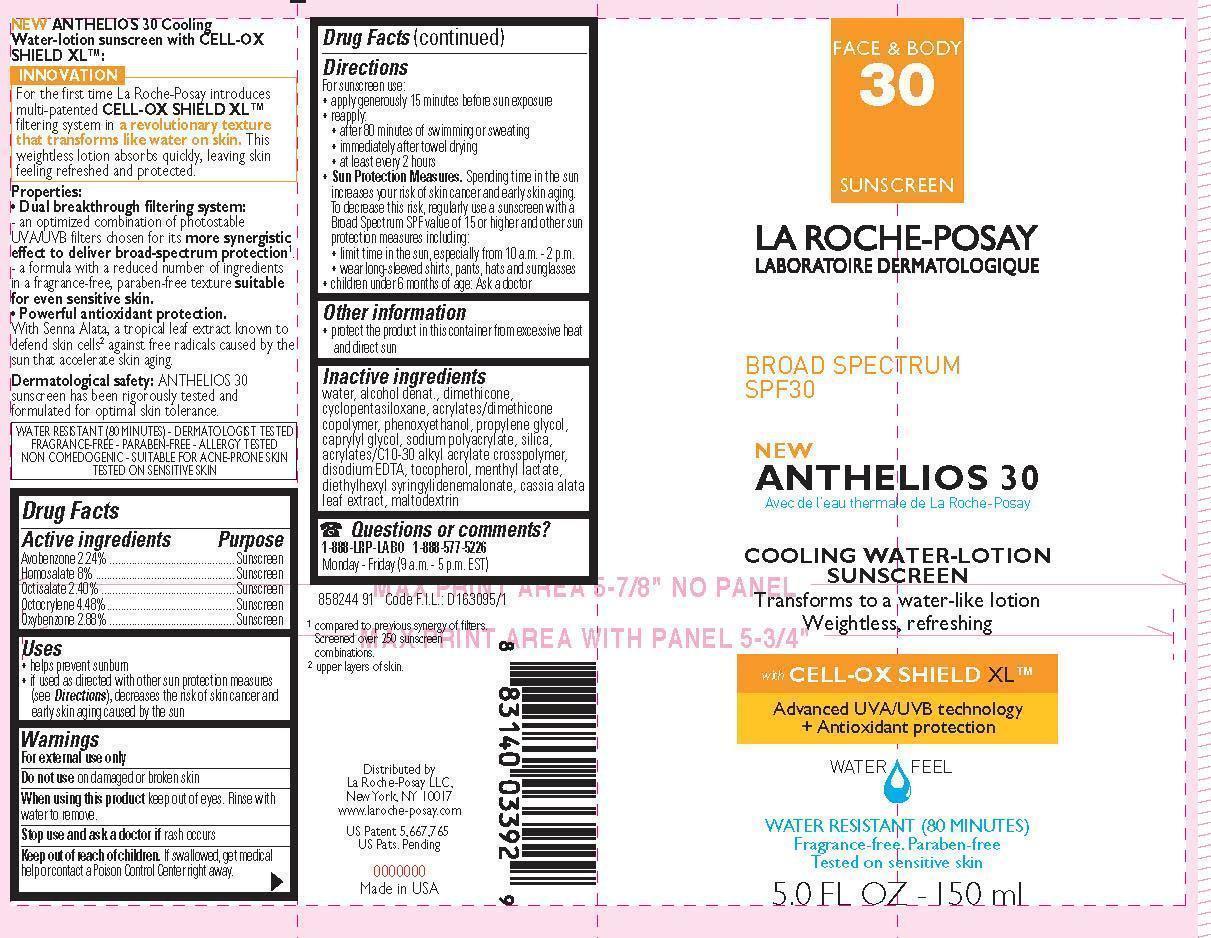 DRUG LABEL: La Roche Posay Laboratoire Dermatologique Anthelios 30 Cooling Water Broad Spectrum SPF 30 Sunscreen
NDC: 49967-392 | Form: LOTION
Manufacturer: L'Oreal USA Products Inc
Category: otc | Type: HUMAN OTC DRUG LABEL
Date: 20231231

ACTIVE INGREDIENTS: AVOBENZONE 22.4 mg/1 mL; HOMOSALATE 80 mg/1 mL; OCTISALATE 24 mg/1 mL; OCTOCRYLENE 44.8 mg/1 mL; OXYBENZONE 28.8 mg/1 mL
INACTIVE INGREDIENTS: WATER; ALCOHOL; DIMETHICONE; PHENOXYETHANOL; PROPYLENE GLYCOL; TOCOPHEROL; DIETHYLHEXYL SYRINGYLIDENEMALONATE; MALTODEXTRIN

Drug Facts

Active ingredients

Avobenzone 2.24%

Homosalate 8%

Octisalate 2.4%

Octocrylene 4.48%

Oxybenzone 2.88%

Purpose

Sunscreen

Uses

- helps prevent sunburn

- if used as directed with other sun protection measures (see Directions), decreases the risk of skin cancer and early skin aging caused by the sun

Warnings

For external use only

Do not use

on damaged or broken skin

When using this product

keep out of eyes. Rinse with water to remove.

Stop use and ask a doctor if

rash occurs

Keep out of reach of children.

If swallowed, get medical help or contact a Poison Control Center right away.

Directions

For sunscreen use:

● apply generously 15 minutes before sun exposure

● reapply:

● after 80 minutes of swimming or sweating

● immediately after towel drying

● at least every 2 hours

● Sun Protection Measures. Spending time in the sun increases your risk of skin cancer and early skin aging. To decrease this risk, regularly use a sunscreen with a Broad Spectrum SPF value of 15 or higher and other sun protection measures including:

● limit time in the sun, especially from 10 a.m. – 2 p.m.

● wear long-sleeved shirts, pants, hats, and sunglasses

● children under 6 months of age: Ask a doctor

Other information

protect the product in this container from excessive heat and direct sun

Inactive ingredients

water, alcohol denat., dimethicone, cyclopentasiloxane, acrylates/dimethicone copolymer, phenoxyethanol, propylene glycol, capryly glycol, sodium polyacrylate, silica, acrylates/C10-30 alkyl acrylate crosspolymer, disodium EDTA, tocopherol, methyl lactate, diethylhexyl syringylidenemalonate, cassia alata leaf extract, maltodextrin

Questions or comments?

1-888-LRP-LAB0 1-888-577-5226

Monday - Friday (9 a.m. - 5 p.m. EST)